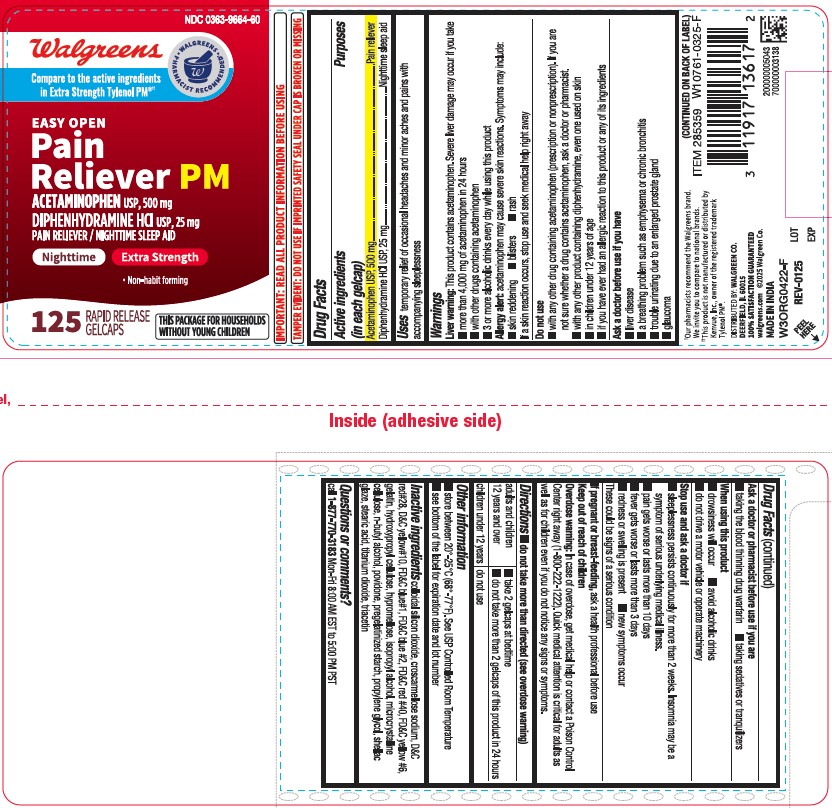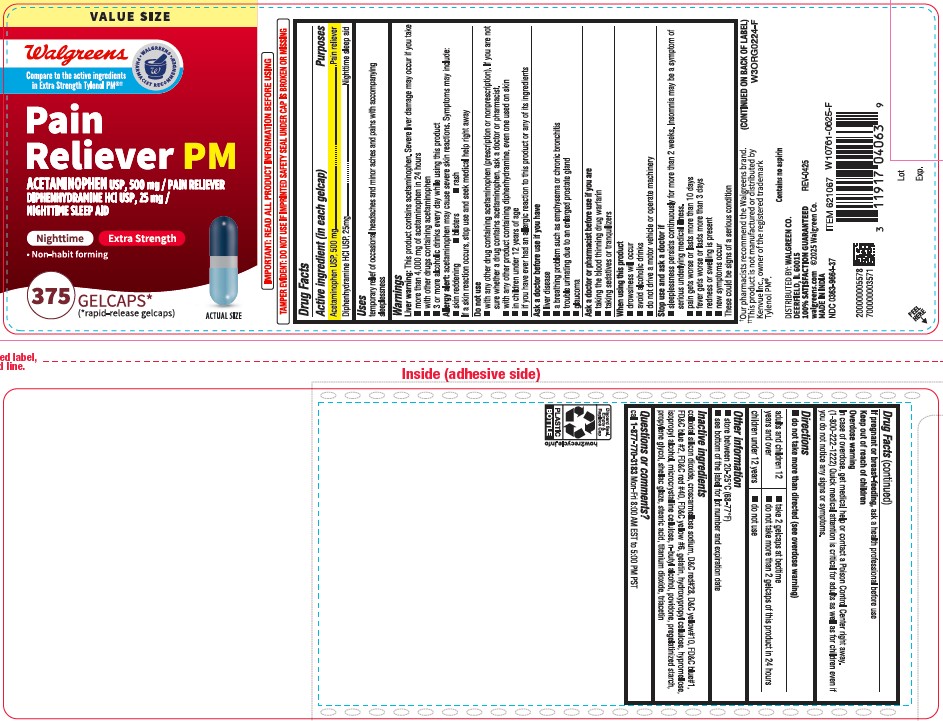 DRUG LABEL: Acetaminophen Diphenhydramine HCL
NDC: 0363-9664 | Form: TABLET
Manufacturer: WALGREENS CO.
Category: otc | Type: HUMAN OTC DRUG LABEL
Date: 20251219

ACTIVE INGREDIENTS: ACETAMINOPHEN 500 mg/1 1; DIPHENHYDRAMINE HYDROCHLORIDE 25 mg/1 1
INACTIVE INGREDIENTS: HYPROMELLOSE 2208 (100 MPA.S); STARCH, CORN; TITANIUM DIOXIDE; FD&C YELLOW NO. 6; STEARIC ACID; CROSCARMELLOSE SODIUM; FD&C RED NO. 40; GELATIN; ISOPROPYL ALCOHOL; MICROCRYSTALLINE CELLULOSE; D&C YELLOW NO. 10; BUTYL ALCOHOL; PROPYLENE GLYCOL; SILICON DIOXIDE; D&C RED NO. 28; FD&C BLUE NO. 1; FD&C BLUE NO. 2; HYDROXYPROPYL CELLULOSE, UNSPECIFIED; POVIDONE; SHELLAC; TRIACETIN

Pain Releiver PM
Acetaminophen USP, 500mg
Diphenhydramine HCL USP, 25mg
PAIN RELIEVER/NIGHTTIME SLEEP AID

Active ingredients (in each gelcap)

Acetaminophen USP, 500mg

Diphenhydramine HCL USP,25mg

Purposes

Pain reliever

Nighttime sleep aid

Uses

temporary relief of occasional headaches and minor aches and pains with accompanying sleeplessness

Liver warning

This product contains acetaminophen. Severe liver damage may occur if you take

■ more than 4,000 mg of acetaminophen in 24 hours

■ with other drugs containing acetaminophen

■ 3 or more alcoholic drinks every day while using this product

Allergy alert

acetaminophen may cause severe skin reactions. Symptoms may include:

■ skin reddening

■ blisters

■ rash

If a skin reaction occurs, stop use and seek medical help right away.

Do not use

■ with any other drug containing acetaminophen (prescription or nonprescription). If you are not sure whether a drug contains acetaminophen, ask a doctor or pharmacist.

■ with any other product containing diphenhydramine, even one used on skin

■ in children under 12 years of age

■ if you have ever had an allergic reaction to this product or any of its ingredients

Ask a doctor before use if you have

■ liver disease

■ a breathing problem such as emphysema or chronic bronchitis

■ trouble urinating due to an enlarged prostate gland

■ glaucoma

Ask a doctor or pharmacist before use if you are

■ taking the blood thinning drug warfarin

■ taking sedatives or tranquilizers

When using this product

■ drowsiness will occur

■ avoid alcoholic drinks

■ do not drive a motor vehicle or operate machinery

Stop use and ask a doctor if

■ sleeplessness persists continuously for more than 2 weeks. Insomnia may be a symptom of serious underlying medical illness.

■ pain gets worse or lasts more than 10 days

■ fever gets worse or lasts more than 3 days

■ redness or swelling is present

■ new symptoms occur

These could be signs of a serious condition.

If pregnant or breast-feeding,

ask a health professional before use.

Keep out of reach of children

Overdose warning

In case of overdose, get medical help or contact a Poison Control Center right away (1-800-222-1222). Quick medical attention is critical for adults as well as for children even if you do not notice any signs or symptoms.

Directions

■ do not take more than directed (see overdose warning)

adults and children 12 years and over

■ take 2 gelcaps at bedtime

■ do not take more than 2 gelcaps of this product in 24 hours

children under 12 years

■ do not use

Other information

■ store between 20°-25°C (68°-77°F). See USP Controlled Room Temperature.

■ see bottom of the label for expiration date and lot number.

Inactive ingredients

colloidal silicon dioxide, croscarmellose sodium, D&C red#28, D&C yellow#10, FD&C blue#1, FD&C blue #2, FD&C red #40, FD&C yellow #6, gelatin, hydroxypropyl cellulose, hypromellose, isopropyl alcohol, microcrystalline cellulose, n-butyl alcohol, povidone, pregelatinized starch, propylene glycol, shellac glaze, stearic acid, titanium dioxide, triacetin.

Questions or comments?

call 1-877-770-3183 Mon-Fri 8:00 AM EST to 5:00 PM PST.